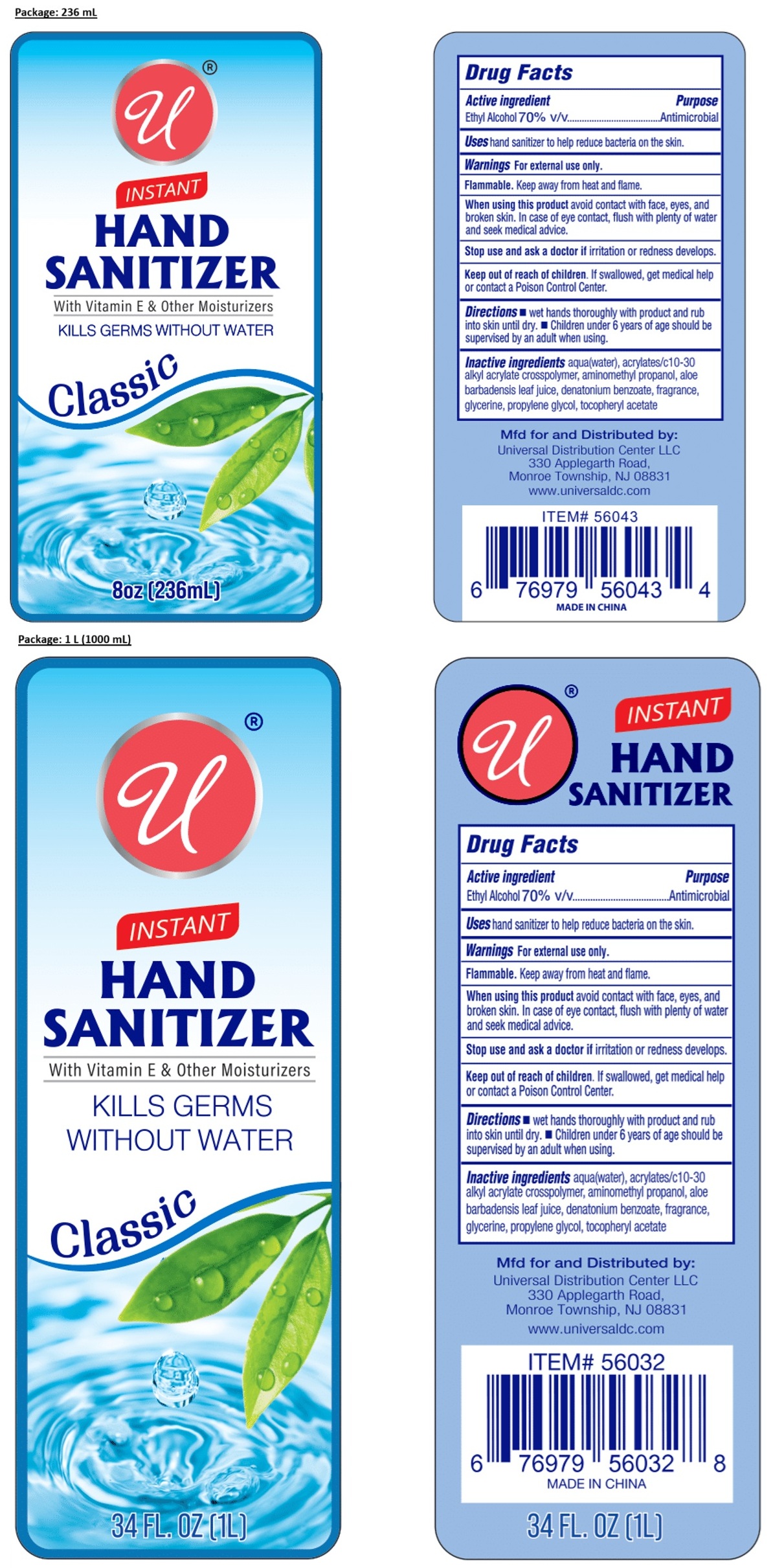 DRUG LABEL: INSTANT HAND SANITIZER Classic
NDC: 52000-434 | Form: LIQUID
Manufacturer: Universal Distribution Center LLC
Category: otc | Type: HUMAN OTC DRUG LABEL
Date: 20251120

ACTIVE INGREDIENTS: ALCOHOL 70 mL/100 mL
INACTIVE INGREDIENTS: WATER; ACRYLATES/C10-30 ALKYL ACRYLATE CROSSPOLYMER (60000 MPA.S); AMINOMETHYLPROPANOL; ALOE VERA LEAF JUICE; DENATONIUM BENZOATE; GLYCERIN; PROPYLENE GLYCOL; .ALPHA.-TOCOPHEROL ACETATE

INSTANT HAND SANITIZER Classic

Active ingredient

Ethyl Alcohol 70% v/v

Purpose

Antimicrobial

Uses

hand sanitizer to help reduce bacteria on the skin.

Warnings

For external use only.

Flammable. Keep away from heat and flame.

When using this product avoid contact with face, eyes, and broken skin. In case of eye contact, flush with plenty of water and seek medical advice.

Stop use and ask a doctor if irritation or redness develops.

Keep out of reach of children. If swallowed, get medical help or contact a Poison Control Center.

Directions

• wet hands thoroughly with product and rub into skin until dry. • Children under 6 years of age should be supervised by an adult when using.

Inactive ingredients

aqua (water), acrylates/c10-30 alkyl acrylate crosspolymer, aminomethyl propanol, aloe barbadensis leaf juice, denatonium benzoate, fragrance, glycerine, propylene glycol, tocopheryl acetate

With Vitamin E & Other Moisturizers

KILLS GERMS WITHOUT WATER

Mfd for and Distributed by:
Universal Distribution Center LLC
330 Applegarth Road,
Monroe Township, NJ 08831

www.universaldc.com

MADE IN CHINA